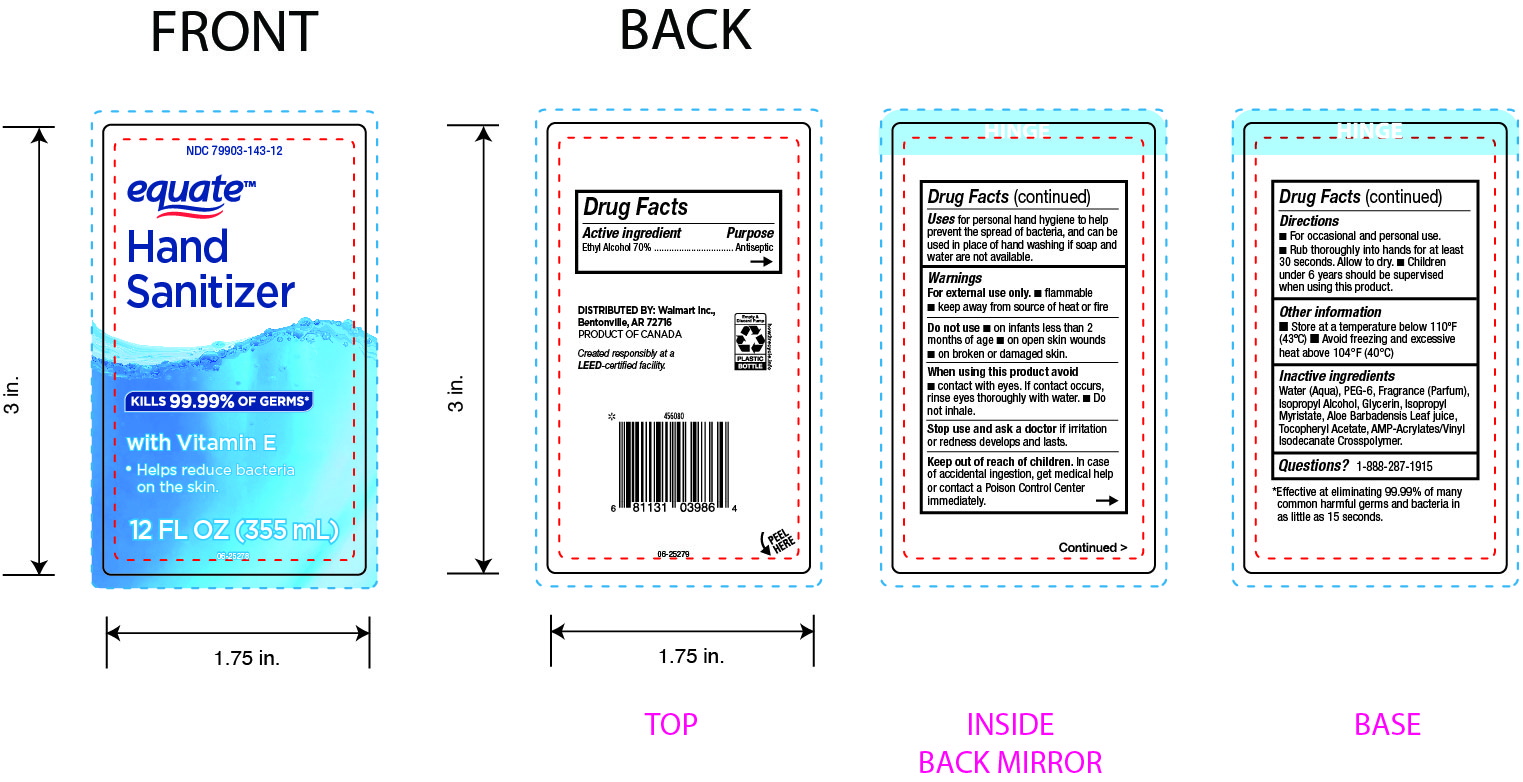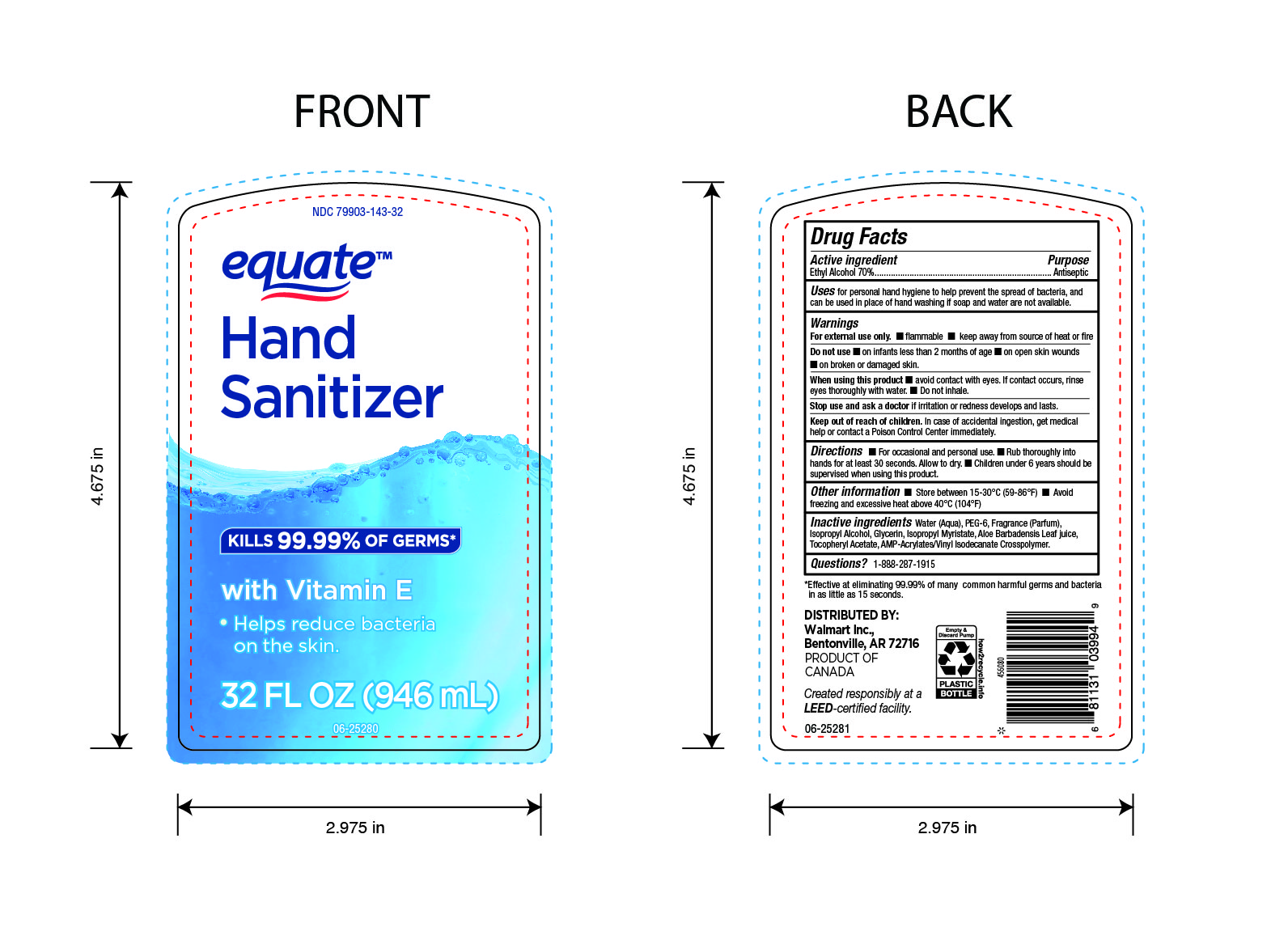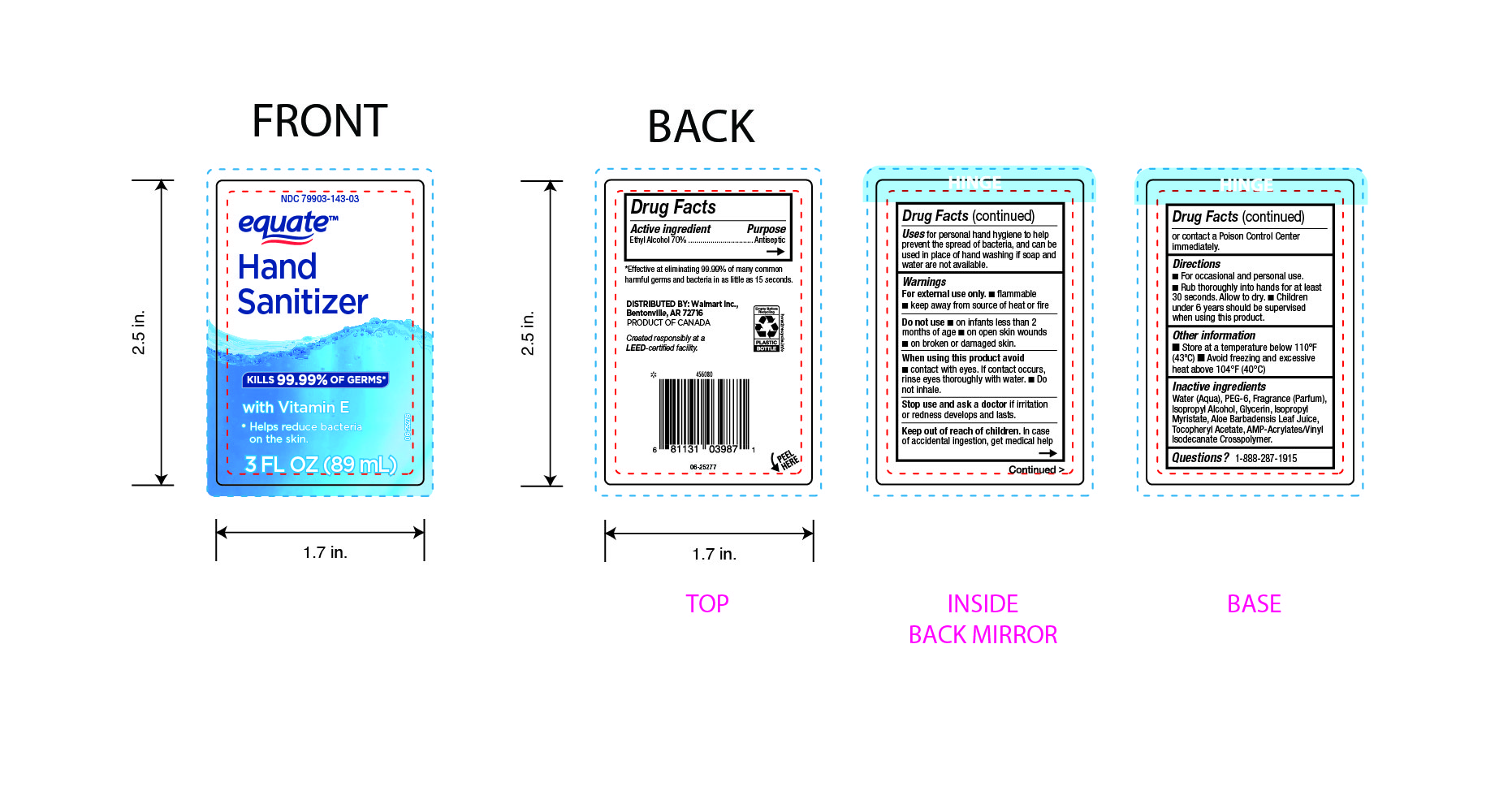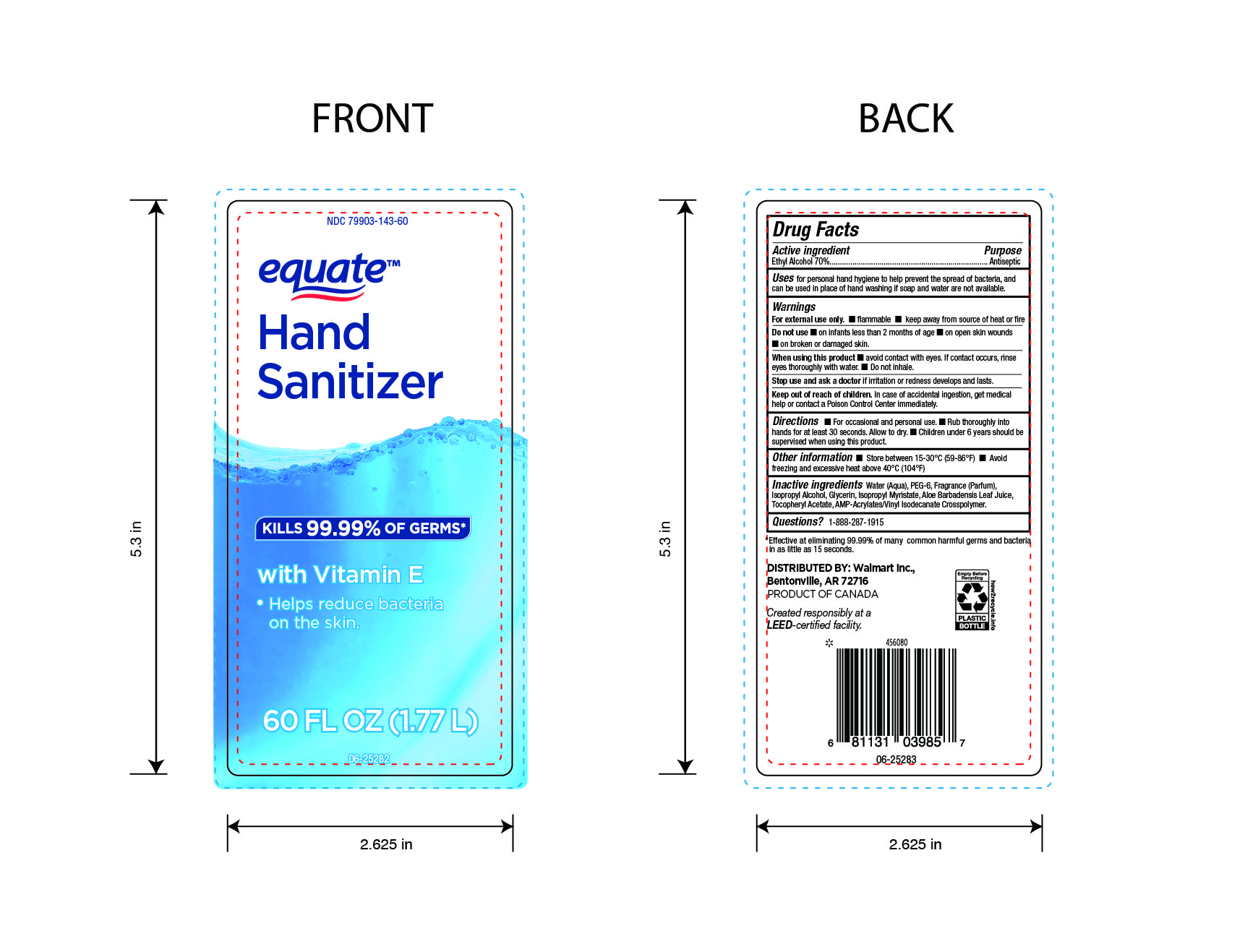 DRUG LABEL: Equate
NDC: 79903-143 | Form: GEL
Manufacturer: Wal-Mart Stores Inc.
Category: otc | Type: HUMAN OTC DRUG LABEL
Date: 20250201

ACTIVE INGREDIENTS: ALCOHOL 700 mg/1 mL
INACTIVE INGREDIENTS: PEG-6; FRAGRANCE CLEAN ORC0600327; ISOPROPYL MYRISTATE; ALOE VERA LEAF; ALPHA-TOCOPHEROL ACETATE; WATER; ISOPROPYL ALCOHOL; GLYCERIN; ACRYLATES/VINYL ISODECANOATE CROSSPOLYMER (10000 MPA.S NEUTRALIZED AT 0.5%)

WalMart sanitizer-79903-143-03

ACTIVE INGREDIENT

Ethyl Alcohol 70%

PURPOSE

Antiseptic

INDICATIONS AND USAGE

Use for personal hand hygiene to help prevent the spread of bacteria, and can be used in place of hand washing if soap and water are not available.

WARNINGS

For external use only - Flammable. Keep away from source of heat or fire.

Do not use ■ on infants less than 2 months of age ■ on open skin wounds
■ on broken or damaged skin.

WHEN USING

■ avoid contact with eyes. If contact occurs, rinse eyes thoroughly with water. ■ Do not inhale

Stop use and ask a doctorif irritation or redness develops and lasts.

Keep out of reach of children. In case of accidental ingestion, get medical help or contact a Poison Control Center immediately.

DOSAGE AND ADMINISTRATION

For occasional and personal use. ■ Rub thoroughly into hands for at least 30 seconds. Allow to dry. ■ Children under 6 years should be supervised when using this product.

STORAGE AND HANDLING

■ Store between 15-30°C (59-86°F) ■ Avoid freezing and excessive heat above 40°C (104°F)

INACTIVE INGREDIENT

Water (Aqua), PEG-6, Fragrance (Parfum), Isopropyl Alcohol, Glycerin, Isopropyl Myristate, Aloe Barbadensis Leaf Juice,
Tocopheryl Acetate, AMP-Acrylates/Vinyl Isodecanate Crosspolymer.